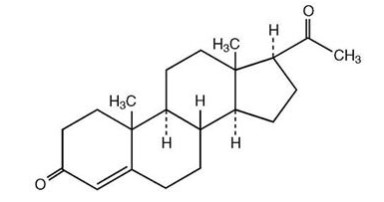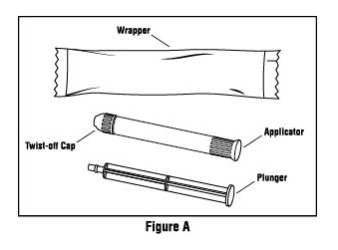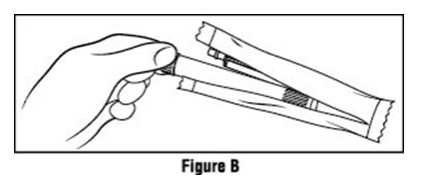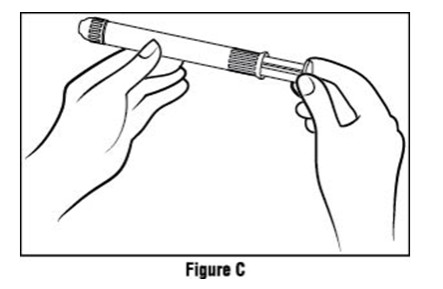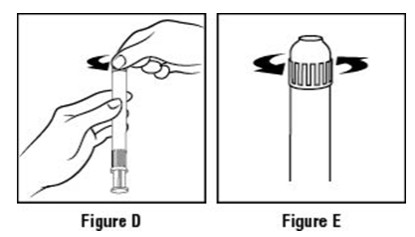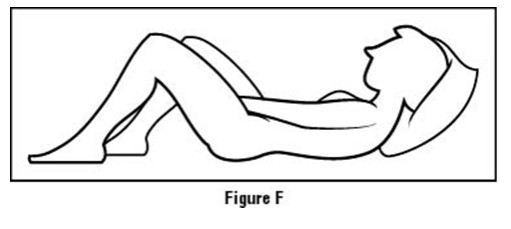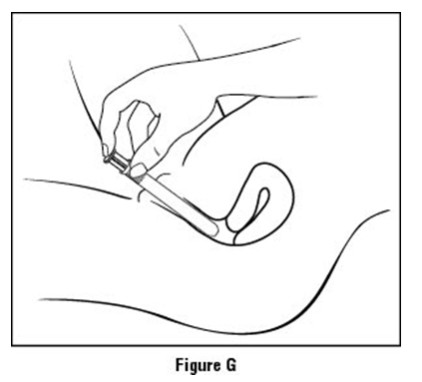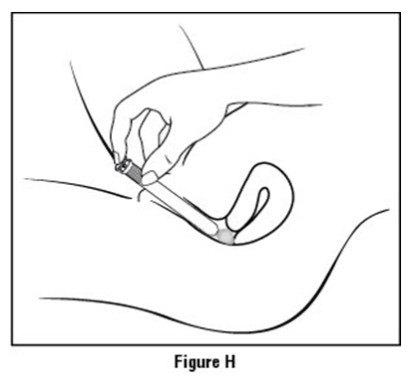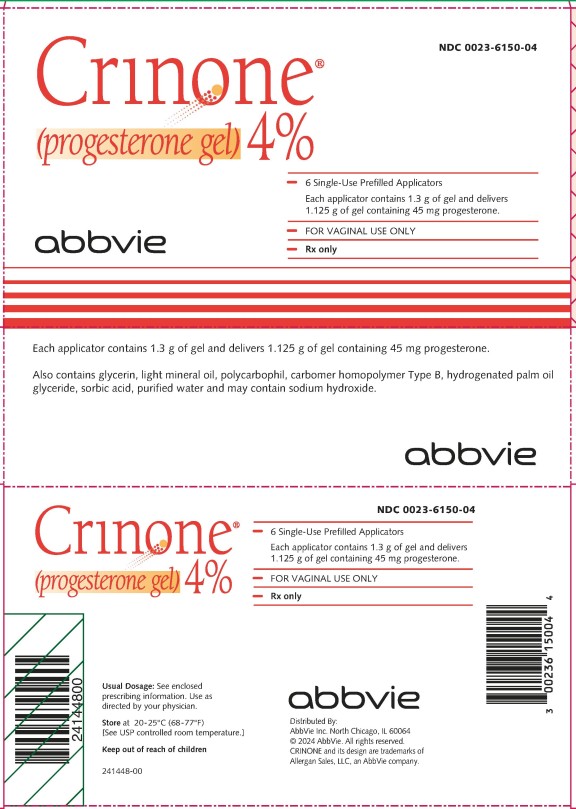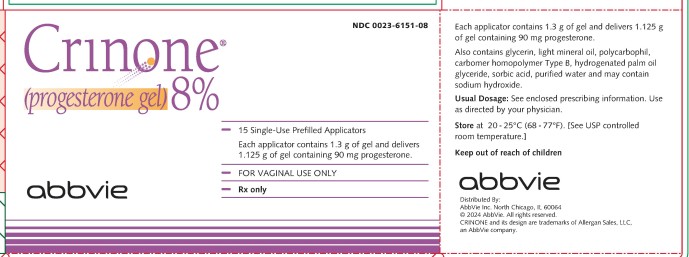 DRUG LABEL: Crinone
NDC: 0023-6150 | Form: GEL
Manufacturer: Allergan, Inc.
Category: prescription | Type: HUMAN PRESCRIPTION DRUG LABEL
Date: 20240521

ACTIVE INGREDIENTS: PROGESTERONE 45 mg/1.125 g
INACTIVE INGREDIENTS: GLYCERIN; LIGHT MINERAL OIL; POLYCARBOPHIL; HYDROGENATED PALM OIL; SORBIC ACID; WATER; SODIUM HYDROXIDE; CARBOMER HOMOPOLYMER TYPE B (ALLYL SUCROSE CROSSLINKED)

Crinone® 4% and Crinone® 8%
(progesterone gel)
PHYSICIAN INFORMATION
For Vaginal Use Only
Rx only

DESCRIPTION

Crinone® (progesterone gel) is a bioadhesive vaginal gel containing micronized progesterone in an emulsion system, which is contained in single use, polypropylene vaginal applicators. The carrier vehicle is an oil in water emulsion containing the water swellable, but insoluble polymer, polycarbophil. The progesterone is partially soluble in both the oil and water phase of the vehicle, with the majority of the progesterone existing as a suspension. Physically, Crinone has the appearance of a soft, white to off-white gel.

The active ingredient, progesterone, is present in either a 4% or an 8% concentration (w/w). The chemical name for progesterone is pregn-4-ene-3,20-dione. It has an empirical formula of C21H30O2 and a molecular weight of 314.5.

The structural formula is:

Progesterone exists in two polymorphic forms. Form 1, which is the form used in Crinone, exists as white orthorhombic prisms with a melting point of 127-131°C.

Each applicator delivers 1.125 grams of Crinone gel containing either 45 mg (4% gel) or 90 mg (8% gel) of progesterone in a base containing glycerin, light mineral oil, polycarbophil, carbomer homopolymer Type B, hydrogenated palm oil glyceride, sorbic acid, purified water and may contain sodium hydroxide.

CLINICAL PHARMACOLOGY

Progesterone is a naturally occurring steroid that is secreted by the ovary, placenta, and adrenal gland. In the presence of adequate estrogen, progesterone transforms a proliferative endometrium into a secretory endometrium. Progesterone is essential for the development of decidual tissue, and the effect of progesterone on the differentiation of glandular epithelia and stroma has been extensively studied. Progesterone is necessary to increase endometrial receptivity for implantation of an embryo. Once an embryo is implanted, progesterone acts to maintain the pregnancy. Normal or near-normal endometrial responses to oral estradiol and intramuscular progesterone have been noted in functionally agonadal women through the sixth decade of life. Progesterone administration decreases the circulatory levels of gonadotropins.

Pharmacokinetics

Absorption

Due to the sustained release properties of Crinone, progesterone absorption is prolonged with an absorption half-life of approximately 25 to 50 hours, and an elimination half-life of 5 to 20 minutes. Therefore, the pharmacokinetics of Crinone are rate-limited by absorption rather than by elimination.

The bioavailability of progesterone in Crinone was determined relative to progesterone administered intramuscularly. In a single dose crossover study, 20 healthy, estrogenized postmenopausal women received 45 mg or 90 mg progesterone vaginally in Crinone 4% or Crinone 8%, or 45 mg or 90 mg progesterone intramuscularly. The pharmacokinetic parameters (mean ± standard deviation) are shown in Table 1.

TABLE 1 Single Dose Relative Bioavailability
 | Crinone 4% | 45 mg Intramuscular Progesterone | Crinone 8% | 90 mg Intramuscular Progesterone
Cmax (ng/mL) | 13.15 ± 6.49 | 39.06 ± 13.68 | 14.87 ± 6.32 | 53.76 ± 14.9
Cavg 0-24 (ng/mL) | 6.94 ± 4.24 | 22.41 ± 4.92 | 6.98 ± 3.21 | 28.98 ± 8.75
AUC0-96 (ng∙hr/mL) | 288.63 ± 273.72 | 806.26 ± 102.75 | 296.78 ± 129.90 | 1378.91 ± 176.39
Tmax (hr) | 5.6 ± 1.84 | 8.2 ± 6.43 | 6.8 ± 3.3 | 9.2 ± 2.7
t1/2 (hr) | 55.13 ± 28.04 | 28.05 ± 16.87 | 34.8 ± 11.3 | 19.6 ± 6.0
F (%) | 27.6 |  | 19.8
Cmax - maximum progesterone serum concentration
Cavg 0-24 - average progesterone serum concentration over 24 hours
AUC0-96 - area under the drug concentration versus time curve from 0-96 hours post dose
Tmax - time to maximum progesterone concentration
t1/2 - elimination half-life
F - relative bioavailability

The multiple dose pharmacokinetics of Crinone 4% and Crinone 8% administered every other day and Crinone 8% administered daily or twice daily for 12 days were studied in 10 healthy, estrogenized postmenopausal women in two separate studies. Steady state was achieved within the first 24 hours after initiation of treatment. The pharmacokinetic parameters (mean ± standard deviation) after the last administration of Crinone 4% or 8% derived from these studies are shown in Table 2.

TABLE 2 Multiple Dose Pharmacokinetics
 | Assisted Reproductive Technology |  | Secondary Amenorrhea
 | Daily Dosing 8% | Twice Daily Dosing 8% | Every Other Day Dosing 4% | Every Other Day Dosing 8%
Cmax (ng/mL) | 15.97± 5.05 | 14.57 ± 4.49 | 13.21± 9.46 | 13.67 ± 3.58
Cavg (ng/mL) | 8.99 ± 3.53 | 11.6 ± 3.47 | 4.05 ± 2.85 | 6.75 ± 2.83
Tmax (hr) | 5.40 ± 0.97 | 3.55 ± 2.48 | 6.67 ± 3.16 | 7.00 ± 2.88
AUC0-t (ng∙hr/mL) | 391.98 ±153.28 | 138.72 ± 41.58 | 242.15 ± 167.88 | 438.36 ± 223.36
t1/2 (hr) | 45.00 ± 34.70 | 25.91 ± 6.15 | 49.87 ± 31.20 | 39.08 ± 12.88

Cmax -maximum progesterone serum concentration
Cavg -average progesterone serum concentration
Tmax -time to maximum progesterone concentration
AUC0-t -area under the drug concentration versus time curve
t1/2 -elimination half-life

Distribution

Progesterone is extensively bound to serum proteins (~ 96-99%), primarily to serum albumin and corticosteroid binding globulin.

Metabolism

The major urinary metabolite of oral progesterone is 5β-pregnan-3α, 20α-diol glucuronide which is present in plasma in the conjugated form only. Plasma metabolites also include 5β-pregnan-3α-ol-20-one (5β-pregnanolone) and 5α-pregnan-3α-ol-20-one (5α-pregnanolone).

Excretion

Progesterone undergoes both biliary and renal elimination. Following an injection of labeled progesterone, 50-60% of the excretion of progesterone metabolites occurs via the kidney; approximately 10% occurs via the bile and feces, the second major excretory pathway. Overall recovery of labeled material accounts for 70% of an administered dose, with the remainder of the dose not characterized with respect to elimination. Only a small portion of unchanged progesterone is excreted in the bile.

CLINICAL STUDIES

Assisted Reproductive Technology

In a single-center, open-label study (COL1620-007US), 99 women (aged 28-47 years) with either partial (n = 84) or premature ovarian failure (n = 15) who were candidates to receive a donor oocyte transfer as an Assisted Reproductive Technology ("ART") procedure were randomized to receive either Crinone 8% twice daily (n = 68) or intramuscular progesterone 100 mg daily (n = 31). The study was divided into three phases (Pilot, Donor Egg and Treatment). The first phase of the study consisted of a test Pilot Cycle to ensure that the administration of transdermal estradiol and progesterone would adequately prime the endometrium to receive the donor egg. The second phase was the Donor Egg Cycle during which a fertilized oocyte was implanted. Crinone 8% was administered beginning the evening of Day 14 of the Pilot and Donor Egg cycles. Subjects with partial ovarian function also underwent a Pre-Pilot Cycle and a Pre-Donor Egg Cycle during which time they were administered only leuprolide acetate to suppress remaining ovarian function. The Pre-Pilot Cycle, Pilot Cycle, Pre-Donor Egg Cycle, and Donor Egg Cycle each lasted approximately 34 days. The third phase of the study consisted of a 10-week treatment period to maintain a pregnancy until placental autonomy was achieved.

Sixty-one women received Crinone 8% as part of the Pilot Cycle to determine their endometrial response. Of the 55 evaluable endometrial biopsies in the Crinone 8% group performed on Day 25 to 27, all were histologically "in-phase", consistent with luteal phase biopsy specimens of menstruating women at comparable time intervals. Fifty-four women who received Crinone 8% and had a histologically "in-phase" biopsy received a donor oocyte transfer. Among these 54 Crinone-treated women, clinical pregnancies (assessed about week 10 after transfer by clinical examination, ultrasound and/or ß-hCG levels) occurred in 26 women (48%). Seventeen women (31%) delivered a total of 25 newborns, seven women (13%) had spontaneous abortions and two women (4%) had elective abortions.

In a second study (COL1620-F01), Crinone 8% was used in luteal phase support of women with tubal or idiopathic infertility due to endometriosis and normal ovulatory cycles, undergoing in vitro fertilization ("IVF") procedures. All women received a GnRH analog to suppress endogenous progesterone, human menopausal gonadotropins, and human chorionic gonadotropin. In this multi-center, open-label study, 139 women (aged 22-38 years) received Crinone 8% once daily beginning within 24 hours of embryo transfer and continuing through Day 30 post-transfer. Clinical pregnancies assessed at Day 90 post-transfer were seen in 36 (26%) of women. Thirty-two women (23%) delivered newborns and four women (3%) had spontaneous abortions. (See PRECAUTIONS, Pregnancy)

Secondary Amenorrhea

In three parallel, open-label studies (COL1620-004US, COL1620-005US, COL1620-009US), 127 women (aged 18-44) with hypothalamic amenorrhea or premature ovarian failure were randomized to receive either Crinone 4% (n = 62) or Crinone 8% (n = 65). All women were treated with either conjugated estrogens 0.625 mg daily (n = 100) or transdermal estradiol (delivering 50 mcg/day) twice weekly (n = 27).

Estrogen therapy was continuous for the entire three 28-day cycle studies. At Day 15 of the second cycle (six weeks after initiating estrogen replacement), women who demonstrated adequate response to estrogen therapy (by ultrasound) and who continued to be amenorrheic received Crinone every other day for six doses (Day 15 through Day 25 of the cycle).

In cycle 2, Crinone 4% induced bleeding in 79% of women and Crinone 8% induced bleeding in 77% of women. In the third cycle, estrogen was continued and Crinone was administered every other day beginning on Day 15 for six doses. On Day 24 an endometrial biopsy was performed. In 53 women who received Crinone 4%, biopsy results were as follows: 7% proliferative, 40% late secretory, 19% mid secretory, 13% early secretory, 7% atrophic, 6% menstrual endometrium, 6% inactive endometrium and 2% negative endometrium. In 54 women who received Crinone 8%, biopsy results were as follows: 44% late secretory, 19% mid secretory, 11% early secretory, 19% atrophic, 5% menstrual endometrium and 2% "oral contraceptive like" endometrium.

INDICATIONS AND USAGE

Assisted Reproductive Technology

Crinone 8% is indicated for progesterone supplementation or replacement as part of an Assisted Reproductive Technology ("ART") treatment for infertile women with progesterone deficiency.

Secondary Amenorrhea

Crinone 4% is indicated for the treatment of secondary amenorrhea. Crinone 8% is indicated for use in women who have failed to respond to treatment with Crinone 4%.

CONTRAINDICATIONS

Crinone should not be used in individuals with any of the following conditions:

1. Known sensitivity to Crinone (progesterone or any of the other ingredients)
2. Undiagnosed vaginal bleeding
3. Liver dysfunction or disease
4. Known or suspected malignancy of the breast or genital organs
5. Missed abortion
6. Active thrombophlebitis or thromboembolic disorders, or a history of hormone-associated thrombophlebitis or thromboembolic disorders

WARNINGS

The physician should be alert to the earliest manifestations of thrombotic disorders (thrombophlebitis, cerebrovascular disorders, pulmonary embolism, and retinal thrombosis). Should any of these occur or be suspected, the drug should be discontinued immediately.

Progesterone and progestins have been used to prevent miscarriage in women with a history of recurrent spontaneous pregnancy losses. No adequate evidence is available to show that they are effective for this purpose.

PRECAUTIONS

General

1. The pretreatment physical examination should include special reference to breast and pelvic organs, as well as Papanicolaou smear.
2. In cases of breakthrough bleeding, as in all cases of irregular vaginal bleeding, nonfunctional causes should be considered. In cases of undiagnosed vaginal bleeding, adequate diagnostic measures should be undertaken.
3. Because progestogens may cause some degree of fluid retention, conditions which might be influenced by this factor (e.g., epilepsy, migraine, asthma, cardiac or renal dysfunction) require careful observation.
4. The pathologist should be advised of progesterone therapy when relevant specimens are submitted.
5. Patients who have a history of psychic depression should be carefully observed and the drug discontinued if the depression recurs to a serious degree.
6. A decrease in glucose tolerance has been observed in a small percentage of patients on estrogen-progestin combination drugs. The mechanism of this decrease is not known. For this reason, diabetic patients should be carefully observed while receiving progestin therapy.

Information for Patients

The product should not be used concurrently with other local intravaginal therapy. If other local intravaginal therapy is to be used concurrently, there should be at least a 6-hour period before or after Crinone administration. Small, white globules may appear as a vaginal discharge possibly due to gel accumulation, even several days after usage.

Drug Interactions

No drug interactions have been assessed with Crinone.

Carcinogenesis, Mutagenesis, Impairment of Fertility

Nonclinical toxicity studies to determine the potential of Crinone to cause carcinogenicity or mutagenicity have not been performed. The effect of Crinone on fertility has not been evaluated in animals.

Pregnancy

[See CLINICAL STUDIES, Assisted Reproductive Technology]

Crinone 8% has been used to support embryo implantation and maintain pregnancies through its use as part of ART treatment regimens in two clinical studies (studies COL1620-007US and COL1620-F01). In the first study (COL1620-007US), 54 Crinone-treated women had donor oocyte transfer procedures, and clinical pregnancies occurred in 26 women (48%). The outcomes of these 26 pregnancies were as follows: one woman had an elective termination of pregnancy at 19 weeks due to congenital malformations (omphalocele) associated with a chromosomal abnormality; one woman pregnant with triplets had an elective termination of her pregnancy; seven women had spontaneous abortions; and 17 women delivered 25 apparently normal newborns.

In the second study (COL1620-F01), Crinone 8% was used in the luteal phase support of women undergoing in vitro fertilization ("IVF") procedures. In this multi-center, open-label study, 139 women received Crinone 8% once daily beginning within 24 hours of embryo transfer and continuing through Day 30 post-transfer.

Clinical pregnancies assessed at Day 90 post-transfer were seen in 36 (26%) of women. Thirty-two women (23%) delivered newborns and four women (3%) had spontaneous abortions. Of the 47 newborns delivered, one had a teratoma associated with a cleft palate; one had respiratory distress syndrome; 44 were apparently normal and one was lost to follow-up.

Geriatric Use

The safety and effectiveness in geriatric patients (over age 65) have not been established.

Pediatric Use

Safety and effectiveness in pediatric patients have not been established.

Nursing Mothers

Detectable amounts of progestins have been identified in the milk of mothers receiving them. The effect of this on the nursing infant has not been determined.

ADVERSE REACTIONS

Assisted Reproductive Technology

In a study of 61 women with ovarian failure undergoing a donor oocyte transfer procedure receiving Crinone 8% twice daily, treatment-emergent adverse events occurring in 5% or more of the women are shown in Table 3.

TABLE 3 Treatment-Emergent Adverse Events in ≥ 5% of Women Receiving Crinone 8% Twice Daily Study COL1620-007US (n = 61)
Body as a Whole
Bloating | 7%
Cramps NOS | 15%
Pain | 8%
Central and Peripheral Nervous System
Dizziness | 5%
Headache | 13%
Gastro-Intestinal System
Nausea | 7%
Reproductive, Female
Breast Pain | 13%
Moniliasis Genital | 5%
Vaginal Discharge | 7%
Skin and Appendages
Pruritus Genital | 5%

In a second clinical study of 139 women using Crinone 8% once daily for luteal phase support while undergoing an in vitro fertilization procedure, treatment-emergent adverse events reported in ≥ 5% of the women are shown in Table 4.

TABLE 4 Treatment-Emergent Adverse Events in ≥ 5% of Women Receiving Crinone 8% Once Daily Study COL1620-F01 (n = 139)
Body as a Whole
Abdominal Pain | 12%
Perineal Pain Female | 17%
Central and Peripheral Nervous System
Headache | 17%
Gastro-Intestinal System
Constipation | 27%
Diarrhea | 8%
Nausea | 22%
Vomiting | 5%
Musculo-Skeletal System
Arthralgia | 8%
Psychiatric
Depression | 11%
Libido Decreased | 10%
Nervousness | 16%
Somnolence | 27%
Reproductive, Female
Breast Enlargement | 40%
Dyspareunia | 6%
Urinary System
Nocturia | 13%

Secondary Amenorrhea

In three studies, 127 women with secondary amenorrhea received estrogen replacement therapy and Crinone 4% or 8% every other day for six doses. Treatment-emergent adverse events during estrogen and Crinone treatment that occurred in 5% or more of women are shown in Table 5.

TABLE 5 Treatment-Emergent Adverse Events in ≥ 5% of Women Receiving Estrogen Treatment and Crinone Every Other Day Studies COL1620-004US, COL1620-005US, COL1620-009US
 | Estrogen + Crinone 4% n = 62 | Estrogen + Crinone 8% n = 65
Body as a Whole
Abdominal Pain | 3 (5%) | 6 (9%)
Appetite Increased | 3 (5%) | 5 (8%)
Bloating | 8 (13%) | 8 (12%)
Cramps NOS | 12 (19%) | 17 (26%)
Fatigue | 13 (21%) | 14 (22%)
Central and Peripheral Nervous System
Headache | 12 (19%) | 10 (15%)
Gastro-Intestinal System
Nausea | 5 (8%) | 4 (6%)
Musculo-Skeletal System
Back Pain | 5 (8%) | 2 (3%)
Myalgia | 5 (8%) | 0 (0%)
Psychiatric
Depression | 12 (19%) | 10 (15%)
Emotional Lability | 14 (23%) | 14 (22%)
Sleep Disorder | 11 (18%) | 12 (18%)
Reproductive, Female
Vaginal Discharge | 7 (11%) | 2 (3%)
Resistance Mechanism
Upper Respiratory Tract Infection | 3 (5%) | 5 (8%)
Skin and Appendages
Pruritus Genital | 1 (2%) | 4 (6%)

OVERDOSAGE

There have been no reports of overdosage with Crinone. In the case of overdosage, however, discontinue Crinone, treat the patient symptomatically, and institute supportive measures.

As with all prescription drugs, this medicine should be kept out of the reach of children.

DOSAGE AND ADMINISTRATION

Assisted Reproductive Technology

Crinone 8% is administered vaginally at a dose of 90 mg once daily in women who require progesterone supplementation. Crinone 8% is administered vaginally at a dose of 90 mg twice daily in women with partial or complete ovarian failure who require progesterone replacement. If pregnancy occurs, treatment may be continued until placental autonomy is achieved, up to 10 to 12 weeks.

Secondary Amenorrhea

Crinone 4% is administered vaginally every other day up to a total of six doses. For women who fail to respond, a trial of Crinone 8% every other day up to a total of six doses may be instituted.

It is important to note that a dosage increase from the 4% gel can only be accomplished by using the 8% gel. Increasing the volume of gel administered does not increase the amount of progesterone absorbed.

HOW SUPPLIED

Crinone is available in the following strengths:

4% gel (45 mg) in a single use, disposable, white polypropylene vaginal applicator with a teal twist-off cap. Each applicator contains 1.3 g of gel and delivers 1.125 g of gel.

NDC 0023-6150-04: 6 Single-use prefilled applicators.

8% gel (90 mg) in a single use, disposable, white polypropylene vaginal applicator with a teal twist-off cap. Each applicator contains 1.3 g of gel and delivers 1.125 g of gel.

NDC 0023-6151-08: 15 Single-use prefilled applicators.
Each applicator is wrapped and sealed in a foil overwrap.
Store at 20-25ºC (68-77ºF). [See USP controlled room temperature.]

Keep out of reach of children.
Rx only

For all medical inquiries contact:
AbbVie Inc.
1-800-678-1605

Distributed by:
AbbVie Inc.
North Chicago, IL 60064

Content Updated: June 2017

© 2024 AbbVie. All rights reserved.

CRINONE and its design are trademarks of Allergan Sales, LLC, an AbbVie company.

PATIENT INFORMATION

Crinone® 4% and Crinone® 8%
(progesterone gel)
For Vaginal Use Only

Please read this information carefully before you start to use Crinone and each time your prescription is renewed, in case anything has changed. This leaflet does not take the place of discussions with your doctor. If you still have any questions, ask your doctor or healthcare provider.

What is Crinone?

Crinone is medicine that contains the female hormone called progesterone.

What is Crinone used for?

- Crinone 4% and Crinone 8% are used to treat the absence of a menstrual period in a woman who has previously had a menstrual period. Progesterone is one of the hormones that allows women to have regular menstrual periods. When you do not produce enough progesterone, menstrual irregularities can occur. Crinone may be prescribed to increase your progesterone.
- Crinone 8% is also used as part of a program for women who are undergoing fertility treatments to get pregnant. Progesterone is one of the hormones that helps to prepare the lining of your uterus so that it is ready to receive and nourish a fertilized egg and to continue a pregnancy. If you are undergoing ART treatment and your doctor has determined your body does not produce enough progesterone on its own, Crinone may be prescribed to increase your progesterone.
- If pregnancy occurs, Crinone may be supplemented for 10 to 12 weeks until production of progesterone by the placenta is adequate.

Who should not use Crinone?
Do not start using Crinone if you:

- Are allergic to progesterone, progesterone-like drugs, or any of the inactive ingredients in the gel (ask a pharmacist if you are not sure about the inactive ingredients in Crinone).
- Have unusual vaginal bleeding which has not been evaluated by a doctor.
- Have or have had a liver disease.
- Have or have had cancer of the breast or genital organs.
- Have had a miscarriage and your physician suspects some tissue is still in the uterus.
- Have or have had blood clots in the legs, lungs, eyes, or elsewhere.

What are the possible side effects of Crinone?
Serious side effects include:

- Blood clots. Progestational drug products may increase your chance of having blood clots in your blood vessels. Blood clots can cause:
  ♦ blood vessel problems (thrombophlebitis)
  ♦ stroke
  ♦ loss of your arm or leg
  ♦ blood clot in your lungs (pulmonary embolus)
  ♦ heart attack
  ♦ death
- Birth defects. Abdominal wall defect and cleft palate have been reported with Crinone use in early pregnancy. It is not known if these defects were caused by Crinone.

Call your healthcare provider right away if you get any of the following warning signs or any other unusual symptoms that concern you:

- Pains in the calves or chest, a sudden shortness of breath or coughing blood indicating possible clots in the legs, heart, or lungs.
- Severe headache or vomiting, dizziness, faintness, or changes in vision or speech, weakness or numbness of an arm or leg indicating possible clots in the brain or eye.

Common side effects include:

- abdominal pain
- perineal pain (the perineum is the area between the vagina and the rectum)
- cramps
- bloating
- headache
- fatigue
- increased appetite
- constipation
- diarrhea
- nausea
- joint pain
- depression
- mood swings
- sleep disorder
- nervousness
- decreased libido
- breast enlargement
- excessive urination at night
- vaginal discharge
- upper respiratory tract infection

These are not all the possible side effects of Crinone. For more information, ask your healthcare provider or pharmacist for advice about side effects. To report SUSPECTED ADVERSE REACTIONS, contact AbbVie at 1-800-678-1605 or FDA at 1-800-FDA-1088 or www.fda.gov/medwatch.

How should I use Crinone?

Use as directed by your healthcare provider.

Read the Instructions for Use included in this leaflet for information on the right way to use Crinone.

Additional information about Crinone

- You may see a small amount of white discharge that may look like a vaginal discharge. This discharge may be caused by gel that can remain in your vagina, even several days after use. Gel discharge from your vagina is normal, but if you are concerned, talk to your healthcare provider.
- If you miss a dose of Crinone, use it as soon as you remember.
- Do not use more Crinone than the dose prescribed by your doctor.
- Talk to your healthcare provider about whether to use other vaginal medicines when you are using Crinone.

General information about the safe and effective use of Crinone

Medicines are sometimes prescribed for purposes other than those listed in a Patient Information Leaflet. Do not use Crinone for another condition. Your doctor has prescribed this drug for you and you alone. Do not give this drug to anyone else, even if they have the same condition.

Keep Crinone out of the reach of children

This leaflet provides the most important information about Crinone. If you would like more information, talk with your healthcare provider or pharmacist. You can ask for information about Crinone that is written for health professionals.

You can get more information by calling the toll free number 1-888-776-4358 or visit www.crinoneusa.com.

What are the ingredients in Crinone?

Crinone contains either 45 mg (4% gel) or 90 mg (8% gel) of progesterone in a base containing glycerin, light mineral oil, polycarbophil, carbomer homopolymer Type B, hydrogenated palm oil glyceride, sorbic acid, purified water and may contain sodium hydroxide.

How should I store Crinone?

Store Crinone at room temperature between 68°F to 77°F (20°C to 25°C).
Do not use Crinone after the expiration date printed on the box.

INSTRUCTIONS FOR USE

Crinone® 4% and Crinone® 8% ("KRI-noan")
(progesterone gel)

For Vaginal Use Only

You will need the following supplies: See Figure A.

Step 1. Remove the applicator from the sealed wrapper.

- Open the sealed wrapper and remove the applicator. Do not remove the twist-off cap at this time. See Figure B.

Step 2. Insert the plunger into the open end of the applicator. See Figure C.

- Hold the applicator on each side and push the plunger into the applicator until the plunger snaps into place.
- You will see about 1 inch of the plunger outside of the applicator.

Step 3. Remove the cap. See Figures D and E.

- Remove the cap from the tip of the applicator by twisting it counterclockwise.
- Do not push the plunger while you are removing the cap. This could cause some gel to come out.

Step 4. Prepare to insert the applicator. See Figure F.

- Choose the position that is most comfortable for you. For example, lying down on your back with your knees bent.

Step 5. Insert the applicator. See Figure G.

- After you are in a comfortable position, gently insert the rounded tip of the applicator into your vagina.

Step 6. Push the plunger. See Figure H.

- While the applicator is inserted in your vagina, push the plunger to release the gel into your vagina.

Step 7. Remove the applicator from your vagina and throw it away in your household trash.

- It is normal for a small amount of gel to be left in the applicator. You will still get the right dose of medicine.

This Instructions for Use has been approved by the U.S. Food and Drug Administration.

Rx only

For all medical inquiries contact:
AbbVie Inc.
1-800-678-1605

Distributed by:
AbbVie Inc.
North Chicago, IL 60064

Content Updated: June 2017

© 2024 AbbVie. All rights reserved.

CRINONE and its design are trademarks of Allergan Sales, LLC, an AbbVie company.

225377-00

PRINCIPAL DISPLAY PANEL

NDC 0023-6150-04
Crinone®
(progesterone gel) 4%
- 6 Single-Use Prefilled Applicators
Each applicator contains 1.3 g of gel and delivers
1.125 g of gel containing 45 mg progesterone.
- FOR VAGINAL USE ONLY
- Rx only
abbvie

PRINCIPAL DISPLAY PANEL

NDC 0023-6151-08
Crinone®
(progesterone gel) 8%
- 15 Single-Use Prefilled Applicators
Each applicator contains 1.3 g of gel and delivers
1.125 g of gel containing 90 mg progesterone.
- FOR VAGINAL USE ONLY
- Rx only
abbvie